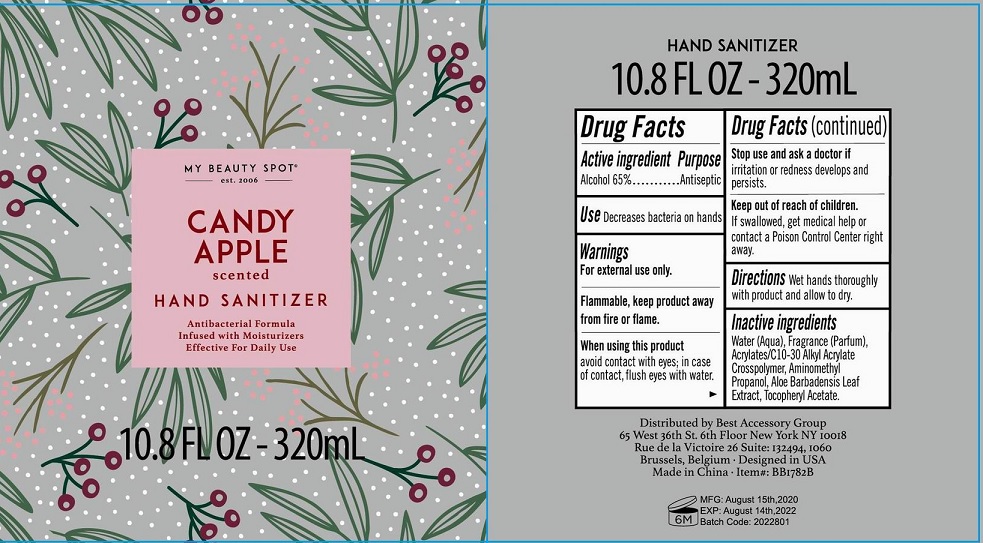 DRUG LABEL: Candy Apple Scented Antibacterial Hand Sanitizer
NDC: 56136-207 | Form: GEL
Manufacturer: Ganzhou Olivee Cosmetic Co., Ltd.
Category: otc | Type: HUMAN OTC DRUG LABEL
Date: 20200923

ACTIVE INGREDIENTS: ALCOHOL 65 mL/100 mL
INACTIVE INGREDIENTS: water; CARBOMER COPOLYMER TYPE A; AMINOMETHYLPROPANOL; GLYCERIN; .ALPHA.-TOCOPHEROL ACETATE, D-

hand sanitizer

Active ingredient

Alcohol 65%

Purpose

Antiseptic

USE

Decrease bacteria on hands

Warnings

For external use only.

When using this product

avoid contact with eyes; in case of contact, flush eyes with water.

Stop use and ask a doctor if

- irritation and redness develops and persists.

Keep out of reach of children.

If swallowed, get medical help or contact a Poison Control Center right away.

Directions

Wet hands thoroughly with product and allow to dry.

Inactive ingredients

Water (Aqua), Acrylates/c 10-30 Alkyl Acrylate Crosspolymer, Aminomethyl Propanol, Fragrace (Parfum), Aloe Barbadensis Leaf Extract, Tocopheryl Acetate